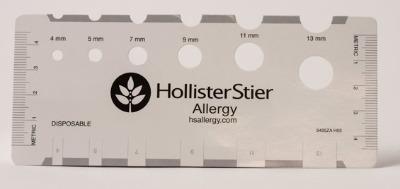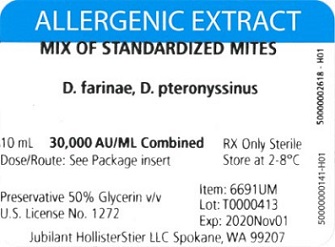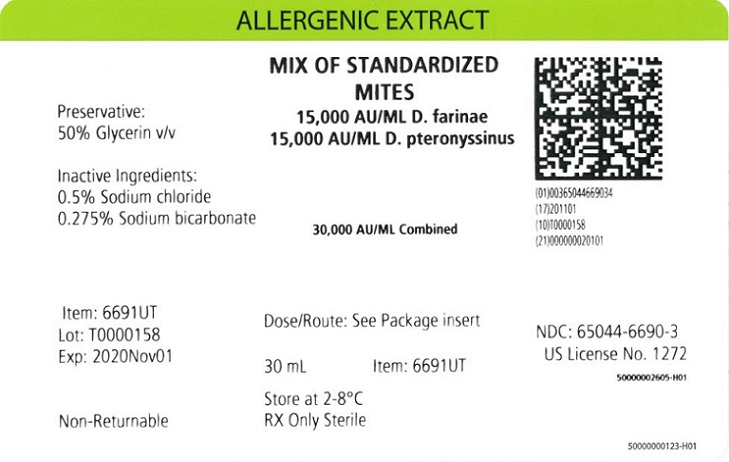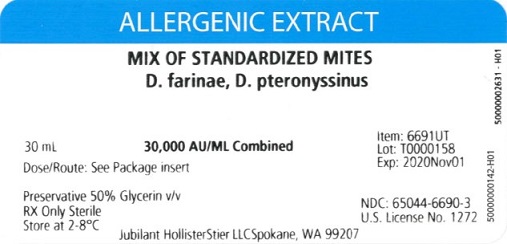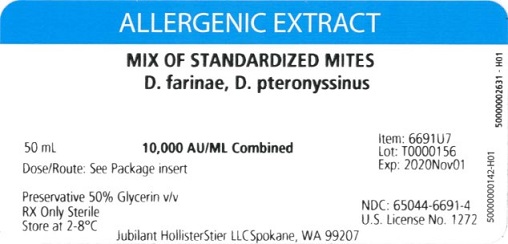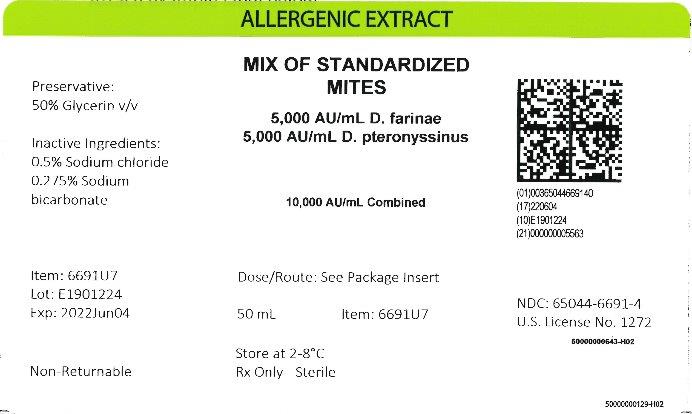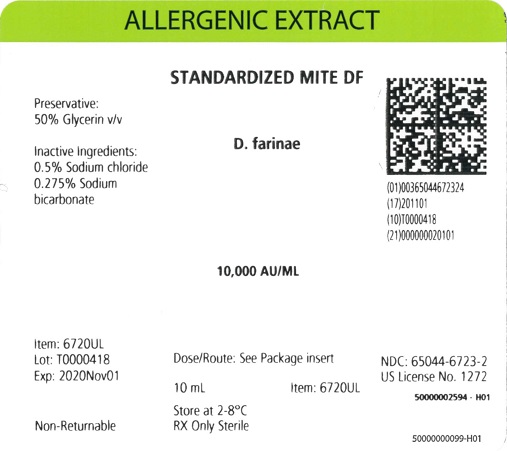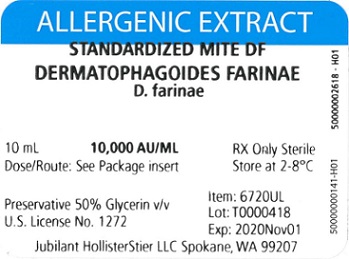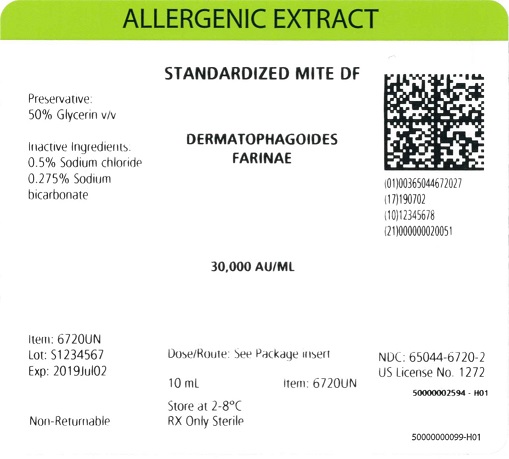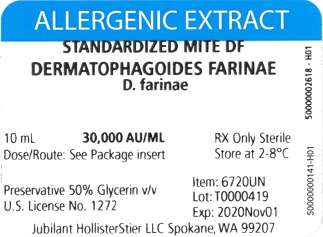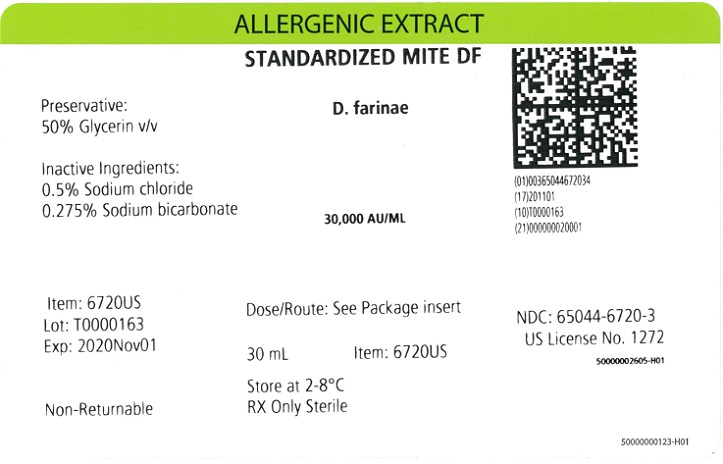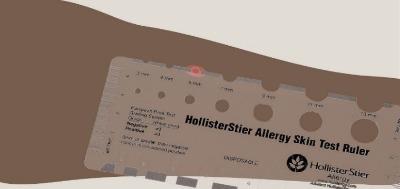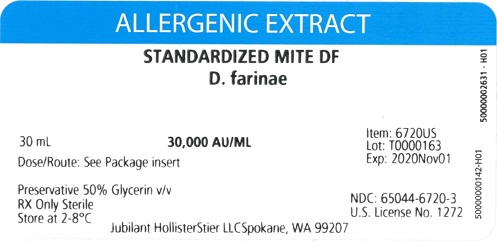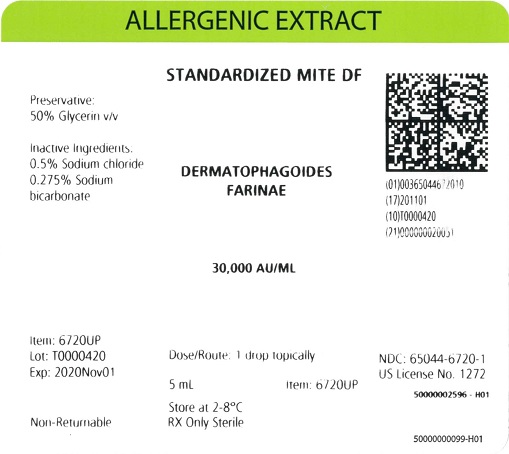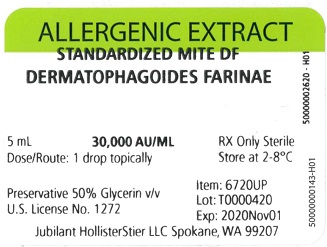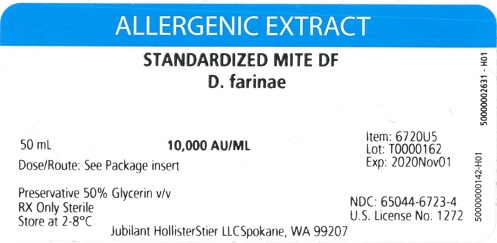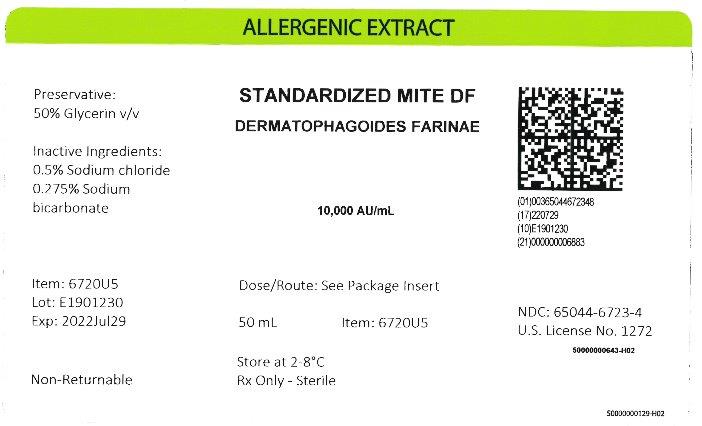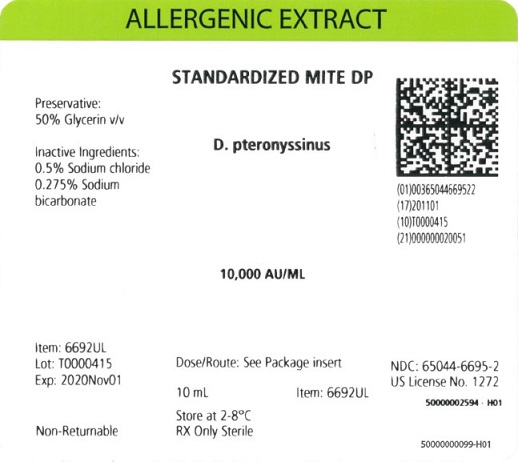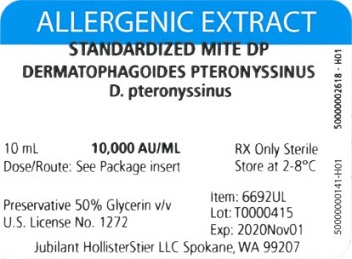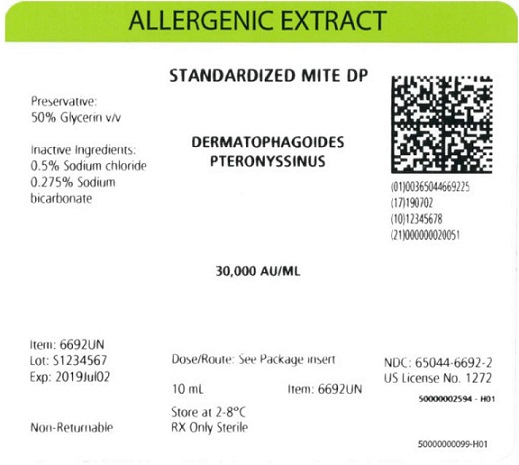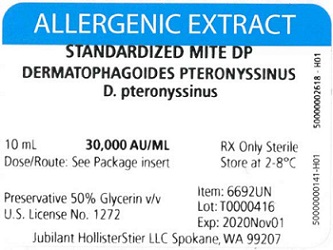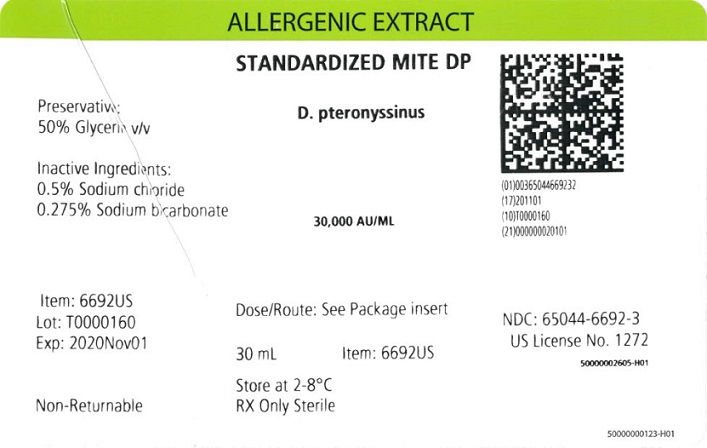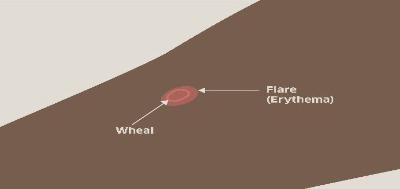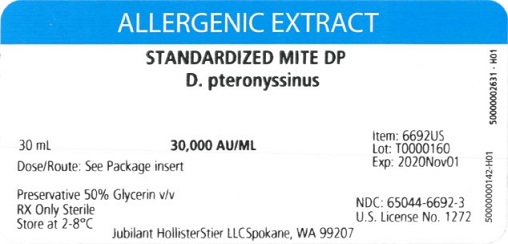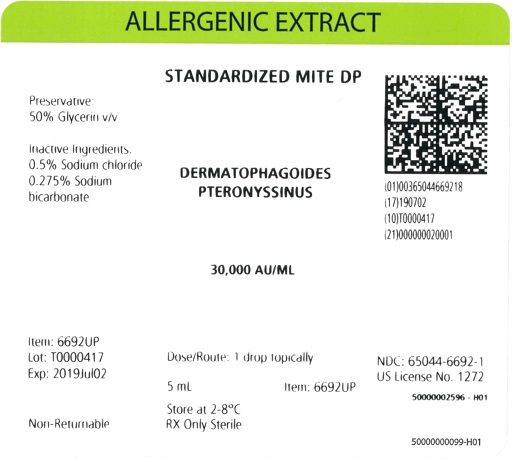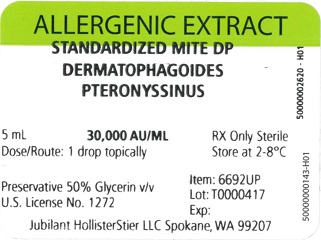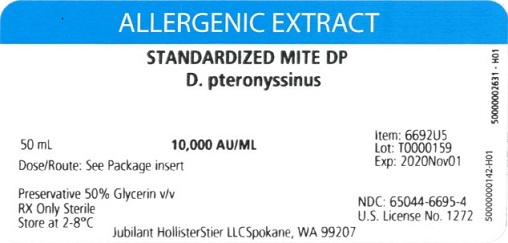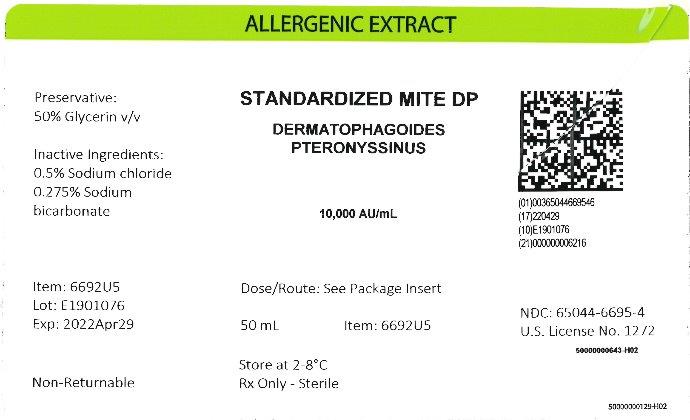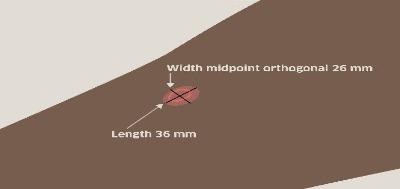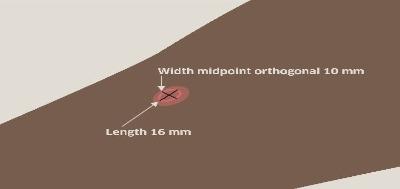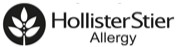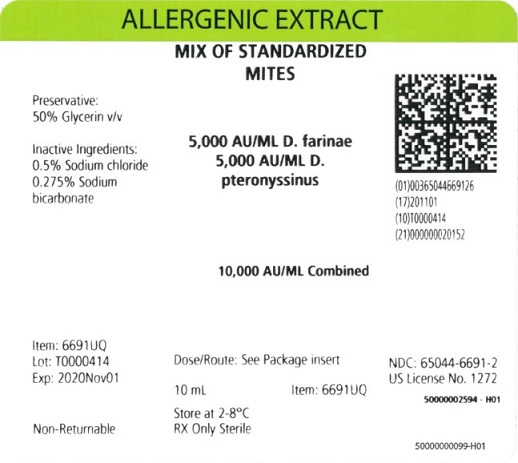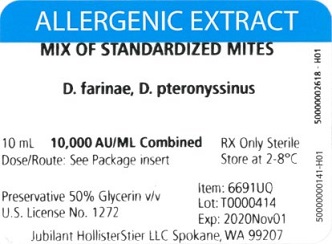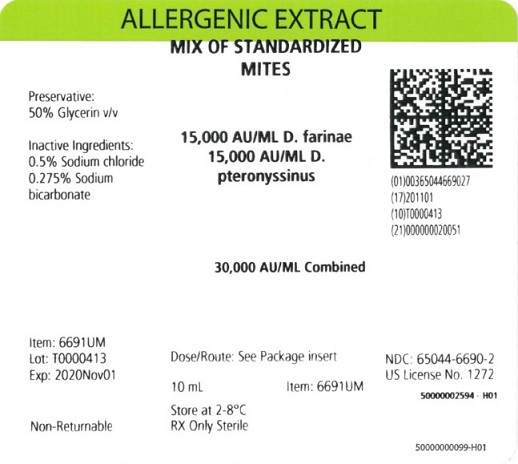 DRUG LABEL: Standardized Mite Mix,  Dermatophagoides pteronyssinus and Dermatophagoides farinae, 10000 AU per mL
NDC: 65044-6691 | Form: INJECTION, SOLUTION
Manufacturer: Jubilant HollisterStier LLC
Category: other | Type: STANDARDIZED ALLERGENIC
Date: 20251119

ACTIVE INGREDIENTS: DERMATOPHAGOIDES FARINAE 5000 [AU]/1 mL; DERMATOPHAGOIDES PTERONYSSINUS 5000 [AU]/1 mL
INACTIVE INGREDIENTS: GLYCERIN; SODIUM CHLORIDE; SODIUM BICARBONATE

HIGHLIGHTS OF PRESCRIBING INFORMATION

These highlights do not include all the information needed to use
STANDARDIZED MITE EXTRACT (Dermatophagoides farinae),
STANDARDIZED MITE EXTRACT (Dermatophagoides pteronyssinus),
and STANDARDIZED MITE MIXTURE EXTRACT (Dermatophagoides farinae and Dermatophagoides pteronyssinus) safely and effectively. See full prescribing information for
STANDARDIZED MITE EXTRACT (Dermatophagoides farinae),
STANDARDIZED MITE EXTRACT (Dermatophagoides pteronyssinus),
and STANDARDIZED MITE MIXTURE EXTRACT (Dermatophagoides farinae and Dermatophagoides pteronyssinus).
STANDARDIZED MITE EXTRACT (Dermatophagoides farinae)
STANDARDIZED MITE EXTRACT (Dermatophagoides pteronyssinus)
STANDARDIZED MITE MIXTURE EXTRACT (Dermatophagoides farinae and Dermatophagoides pteronyssinus)
Injection, for percutaneous, intradermal, or subcutaneous use. Initial U.S. Approval: 1988
August 2024
345014-H08

WARNING: ANAPHYLAXIS

See full prescribing information for complete boxed warning.

- Standardized Mite Extract (Dermatophagoides farinae), Standardized Mite Extract (Dermatophagoides pteronyssinus), Standardized Mite Mixture Extract (Dermatophagoides farinae and Dermatophagoides pteronyssinus) can cause anaphylaxis, including anaphylactic shock and death. (5.1)
- Do not administer to individuals with severe, unstable or uncontrolled asthma, history of severe systemic reaction to the allergen extract when administered for diagnosis or treatment, or with medical conditions that reduce the ability to survive anaphylaxis. (4)
- Observe individuals for at least 30 minutes following administration. Emergency measures and healthcare providers trained in their use must be available in the event of a life-threatening reaction. (5.1)
- Individuals with extreme sensitivity to these products, on an accelerated immunotherapy build-up, switching to another lot, receiving high doses of these products, or exposed to excessive amounts of dust mite may be at increased risk of anaphylaxis. (5.1)
- These products may not be suitable for individuals who may be unresponsive to epinephrine or inhaled bronchodilators, such as those taking beta-blockers. (5.1)

1 INDICATIONS AND USAGE

Standardized Mite Extract (Dermatophagoides farinae), and Standardized Mite Extract (Dermatophagoides pteronyssinus) are skin tests indicated for:

- Diagnosis of patients with a clinical history of allergy to dust mite allergens.

Standardized Mite Extract (Dermatophagoides farinae), Standardized Mite Extract (Dermatophagoides pteronyssinus), Standardized Mite Mixture Extract (Dermatophagoides farinae and Dermatophagoides pteronyssinus) (standardized mite extracts) are immunotherapies indicated for:

- Mitigation of mite-induced allergic asthma, rhinitis and conjunctivitis in patients with hypersensitivity to dust mites based on clinical history and confirmation by skin or in vitro testing for allergen-specific IgE antibodies.

2 DOSAGE AND ADMINISTRATION

For percutaneous, intradermal, or subcutaneous use only.

Administration:

- Percutaneous for diagnostic testing
- Intradermal for diagnostic testing
- Subcutaneous for immunotherapy

See full prescribing information for details on dosing and dilution preparation. (2)

3 DOSAGE FORMS AND STRENGTHS

Injection. Standardized mite extracts are labeled in Allergenic Units per milliliter (AU/mL). (11)

Refer to the vial label for the product concentration. (16)

- For percutaneous testing, standardized mite extract stock concentrates containing 30,000 AU/mL of D. farinae or D. pteronyssinus are supplied in 5 mL dropper vials. (11)
- For intradermal testing, standardized mite extract stock concentrates containing 30,000 AU/mL of D. farinae or D. pteronyssinus are supplied in 10 mL and 30 mL multidose vials. (11)
- For immunotherapy, standardized mite extract stock concentrates containing a total of 10,000 or 30,000 AU/mL of D. farinae or D. pteronyssinus or 5,000 or 15,000 AU/ml of an equal mixture of D. farinae and D. pteronyssinus are supplied in 10, 30, and 50 mL multiple-dose vials. (11)

4 CONTRAINDICATIONS

- Severe, unstable or uncontrolled asthma. (4)
- History of any severe systemic reaction to the allergen extract when administered for diagnosis or treatment. (4)
- Medical conditions that reduce the ability to survive anaphylaxis. (4)

5 WARNINGS AND PRECAUTIONS

The risk of anaphylaxis may be increased in the following situations:

- Extreme sensitivity to standardized mite extracts.
- Receipt of an accelerated build-up schedule.
- Change from one lot of a particular standardized mite extract to another lot of the same standardized mite extract.
- Receipt of high doses of the standardized mite extracts.
- Exposure to excessive amounts of dust mite.

6 ADVERSE REACTIONS

Common adverse reactions reported for standardized mite extracts are:

- Local adverse reactions, occurring in 26 to 82 % of all patients who receive subcutaneous immunotherapy (e.g., erythema, swelling, pruritus, tenderness and pain at the injection site). (6)
- Systemic adverse reactions, occurring in ≤ 7 % of patients who receive subcutaneous immunotherapy (e.g., generalized skin erythema, urticaria, pruritus, angioedema, rhinitis, wheezing, laryngeal edema, hypotension, and shock). Systemic reactions may be fatal. (6)

To report SUSPECTED ADVERSE REACTIONS, contact Jubilant HollisterStier at 1-800-495-7437 or Adverse.Reactions@jubl.com; or the FDA at 1-800-FDA-1088 or www.fda.gov/medwatch.

7 DRUG INTERACTIONS

Certain medications may decrease skin test wheal and erythema responses, including antihistamines (7.1), topical corticosteroids/topical anesthetics (7.2), tricyclic antidepressants (7.3).

FULL PRESCRIBING INFORMATION

WARNING: ANAPHYLAXIS

- Standardized Mite Extract (Dermatophagoides farinae), Standardized Mite Extract (Dermatophagoides pteronyssinus), Standardized Mite Mixture Extract (Dermatophagoides farinae and Dermatophagoides pteronyssinus) can cause anaphylaxis, including anaphylactic shock and death.^1 (5.1)
- Do not administer to individuals with:

- severe, unstable or uncontrolled asthma;

- history of severe systemic reaction to the allergen extract when administered for diagnosis or treatment;

- medical conditions that reduce the ability to survive anaphylaxis. (4)

- Observe individuals for at least 30 minutes following administration. Emergency measures and healthcare providers trained in their use must be available in the event of a life-threatening reaction. (5.1)
- Individuals with extreme sensitivity to these products, on an accelerated immunotherapy build-up, switching to another lot, receiving high doses of these products, or exposed to similar allergens may be at increased risk of anaphylaxis. (5.1)
- These products may not be suitable for individuals who may be unresponsive to epinephrine or inhaled bronchodilators, such as those taking beta-blockers. (5.1)

1 INDICATIONS AND USAGE

Standardized Mite Extract (Dermatophagoides farinae), and Standardized Mite Extract (Dermatophagoides pteronyssinus) are skin tests indicated for:

- Diagnosis of patients with a clinical history of allergy to dust mite allergens. ^(8, 9, 10, 13)

Standardized Mite Extract (Dermatophagoides farinae), Standardized Mite Extract (Dermatophagoides pteronyssinus), Standardized Mite Mixture Extract (Dermatophagoides farinae and Dermatophagoides pteronyssinus) are immunotherapies indicated for:

- Mitigation of mite-induced allergic asthma, rhinitis and conjunctivitis in patients with hypersensitivity to dust mites based on clinical history and confirmation by skin or in vitro testing for allergen-specific IgE antibodies.^(11, 12)

2 DOSAGE AND ADMINISTRATION

2.1 Preparation for Administration

Appearance is clear to slightly opalescent. Standardized mite extracts should be a yellowish to light brown solution. Parenteral drug products should be inspected visually for particulate matter and discoloration prior to administration, whenever solution and container permit. Discard solution if either of these conditions exist.

Standardized mite extracts diluted with Albumin Saline with Phenol (0.4 %) (stabilized diluent) may be more potent than standardized mite extracts diluted with diluents that do not contain albumin. When switching from non-stabilized to stabilized diluent, consider less concentrated initial dilutions for both intradermal testing and immunotherapy.

Different formulations, preparations, or new lots of standardized mite extracts are not interchangeable. Dosage should be adjusted appropriately when formulations, preparations, or lots of standardized mite extracts are changed [see Immunotherapy (2.3) and Dosage Forms and Strengths (3)].

Standardized mite extracts may be prepared for intradermal (diagnosis) or subcutaneous (immunotherapy) administration by diluting stock concentrates.

- For diluent, use sterile albumin saline with phenol or sterile normal saline with phenol.
- Dilute stock concentrates by a minimum of 100-fold for intradermal testing. Dilutions of 1,000-fold or greater are appropriate starting points for patients with a clinical history of adverse reaction.

To prepare dilutions for intradermal testing and immunotherapy, start with a stock concentrate, and prepare a ten-fold (1:10) dilution by adding 0.5 mL of concentrate to 4.5 mL of sterile aqueous diluent. Prepare subsequent dilutions in a similar manner (see Table 1).

Table 1: 10-fold Dilution Series for Standardized Mite Extracts Labeled 10,000 AU*/mL and 30,000 AU*/mL

Dilution** | Extract | Milliliters of Diluent | Dilution Strength AU/mL | Dilution Strength AU/mL
0 | Concentrate | 0 | 10,000 | 30,000
1 | 0.5mL Concentrate | 4.5 | 1,000 | 3,000
2 | 0.5mL Dilution 1 | 4.5 | 100 | 300
3 | 0.5mL Dilution 2 | 4.5 | 10 | 30
4 | 0.5mL Dilution 3 | 4.5 | 1 | 3
5 | 0.5mL Dilution 4 | 4.5 | 0.1 | 0.3
6 | 0.5mL Dilution 5 | 4.5 | 0.01 | 0.03
7 | 0.5mL Dilution 6 | 4.5 | 0.001 | 0.003

* Allergy Units

** Store extract dilutions at 2 °C to 8 °C (36 °F to 46 °F).

2.2 Diagnostic Testing

For percutaneous and intradermal use only.

Use Standardized Mite Extract (Dermatophagoides farinae) or Standardized Mite Extract (Dermatophagoides pteronyssinus) to identify patients who exhibit an allergic response to either species of dust mite (D. farinae or D. pteronyssinus). False positive reactions may occur. A positive skin test reaction must be interpreted in the context of the individual’s clinical history and known exposure to the allergen.

- Administer percutaneous tests prior to administration of intradermal tests.
- Do not use Standardized Mite Mixture Extract (Dermatophagoides farinae and Dermatophagoides pteronyssinus) for diagnostic testing because a positive reaction would not permit identification of the specific mite allergen that elicited the reaction. In addition, a negative reaction would fail to indicate whether an individual component allergen would have elicited a positive reaction at full strength.

Percutaneous Skin Testing

Dose

Unless an individual is suspected to be at greater risk for anaphylaxis, the initial starting dose is 1 drop (approximately 0.05 mL) of concentrated standardized mite extract (30,000 AU/mL). For individuals suspected to be at greater risk for anaphylaxis (for example, as indicated by a history of allergen-induced anaphylaxis), initiate percutaneous testing with 1 drop of a diluted standardized mite extract, if negative retest with the next higher concentration(s). Doses should be administered 15‑20 minutes apart [see Preparation for Administration (2.1)].

Administration

Place one drop (approximately 0.05 mL) of standardized mite extract on the skin and using a skin test device, such as a sterile needle, lancet, or bifurcated needle, pierce through the drop into the skin with a slight lifting motion.

For self-loading devices refer to the manufacturer’s product instructions.

Include a positive histamine skin test control to identify patients whose recent use of drugs with antihistamine activity may result in a false negative skin test. [see Drug Interactions (7.1)].

Include a negative control to detect false positive responses, which can occur when the patient has a non-specific reaction to the diluent or due to dermographism. A 50% glycerin solution may be used as the negative control.

Interpreting Results

Measure and record skin test responses 15-20 minutes after exposure.^22 Individual patient reactivity can vary with time, allergen potency, and/or immunotherapy, as well as testing technique. The most reliable method of recording a skin test reaction is to measure the largest diameter of both wheal and erythema. While some correlation exists between the size of the skin test reaction and the degree of sensitivity, other factors should be considered in the diagnosis of allergy to specific allergens (see Figure 1).

- The negative control (50 % glycerin solution) response should measure < 3 mm wheal and ≤ 10 mm flare.
- Response to the positive control should be at least 3 millimeters larger than the response to the negative control.
- If either the response to the histamine positive control or to the negative control do not meet the criteria above for acceptable wheal size, the results for the allergenic extracts tested at the same time should be considered invalid and be repeated.

Figure 1: Measurement of Wheal and Flare

Use a paper or plastic millimeter skin reaction guide as shown below.

Fifteen minutes after application of the skin test, measure the length and midpoint orthogonal width of each flare and wheal from the inner edge of the reaction.

The wheal is a smooth, slightly elevated area which is redder or paler than the surrounding skin. The flare is the red outermost zone of the skin test reaction.

The length of the skin test is defined as the largest diameter and the width of the skin test is defined as the diameter perpendicular to the length at its midpoint. Consider the wheal and flare as separate entities. First, measure the flare and then independently measure the wheal.

Measuring the Flare Measuring the Wheal

The average diameter measurement in the example above of the flare is (26 mm + 36 mm)/2 = 31 mm and the average diameter of the wheal is (10 mm + 16 mm)/2 = 13 mm.

Intradermal (Intracutaneous) Skin Testing

Always perform percutaneous tests prior to intradermal skin tests.^22

Dose

For patients with negative or equivocal percutaneous testing for whom there is a high index of suspicion of dust mite allergy, intradermal testing may be performed with 0.02 to 0.05 mL of a 30 AU/mL extract solution. [see Preparation for Administration (2.1)]. If this test is negative, a second intradermal test may be performed with 0.02 to 0.05 mL of a 300 AU/mL extract solution.

Administration

Intradermally inject the dose of the diluted allergenic extract using a 1 mL syringe.

Include a positive histamine control at intradermal strength to identify patients whose recent use of drugs with antihistamine activity may result in a false negative skin test. [see Drug Interactions (7.1)].

Include an aqueous buffer negative control (Sterile Albumin Saline with Phenol, Sterile Buffered Saline with Phenol) to detect false positive responses, which can occur when the patient has a non-specific reaction to the diluent or due to dermographism.

Interpreting Results

Measure wheal responses for the histamine positive control test and allergen tests at 15‑20 minutes after injection. Refer to Figure 1 for the measurement of wheal and flare.

- Response to the positive control should be at least 3 millimeters larger than the response to the negative control.
- The negative control (sterile aqueous diluent) response should measure < 3 mm wheal and ≤ 10 mm flare (erythema).

- If either the response to the histamine positive control or to the negative control do not meet the criteria above for acceptable wheal size, the results for the allergenic extracts tested at the same time should be considered invalid and be repeated.

2.3 Immunotherapy

For subcutaneous use only.

Subcutaneous injections for immunotherapy should be prepared by dilution of stock concentrate. See Table 1 for dilution preparation.

Administration

Administer immunotherapy by subcutaneous injection in the lateral aspect of the arm or thigh. Do not inject directly into any blood vessels.

Most adverse reactions occur within 30 minutes after injection. Therefore, observe patients for at least 30 minutes.^23

Dose Build-up

Dosing of standardized mite extracts for allergen immunotherapy is highly individualized. The initial dose should be based on the patient’s percutaneous skin test reactivity and clinical history. The initial dose is typically 0.05 mL of a 0.01 to 0.03 AU/mL dilution. In patients who appear to be exquisitely sensitive by skin test and history, consider a lower initial dose such as 0.05 mL of a 0.001 to 0.003 AU/mL dilution. The dose is increased at each injection by no more than 50% of the previous dose, and the next increment is governed by the response to the last injection. Dosing is increased in increments until 0.5 mL is reached, following which 0.05 mL is administered from the next most concentrated allergen extract or allergen mixture vial in the dilution series. Injections are typically given one or two times per week until the maintenance dose is reached.

- Any evidence of a systemic reaction to immunotherapy is an indication for a significant reduction (at least 75%) in the subsequent dose or the cessation of immunotherapy. Proceed cautiously in subsequent dosing if immunotherapy is continued.
- Repeated systemic reactions, even of a mild nature, are sufficient reason for the cessation of further attempts to increase the reaction-causing dose.
- The volume of solution for immunotherapy may produce increased discomfort in pediatric individuals. In order to achieve the total dose required, the volume of the dose may be divided into more than one injection per visit.
  Maintenance Dose Selection and Intervals
  Select a maintenance dose based on the patient's clinical response and tolerance.
- Typical maintenance dose is 500-2,000 AU.^23 Occasionally, higher doses are necessary to relieve symptoms.
- The two mite species are highly cross-reactive. Therefore, consider the total Allergy Units when determining the target maintenance dose.
- Maintenance doses larger than 0.2 mL of undiluted allergen extract are rarely administered because an extract in 50% glycerin may cause patient discomfort upon injection.
- After the maintenance dose is achieved, increase the injection interval to 2 weeks, then 3 weeks, and finally 4 weeks as tolerated. The optimal interval between maintenance doses of allergenic extract varies among individuals. Administer the maintenance dose at a given interval three or four times before further increasing the interval to ensure that no reactions occur. Protection may be lost rapidly if the interval between doses is more than 4 weeks.
  Dosage Modification for Immunotherapy
  Withhold immunotherapy and/or reduce dosage, if any of the following conditions exist:
- Severe symptoms of rhinitis and/or asthma.
- Infection accompanied by fever.

Any evidence of a systemic reaction is an indication for a significant reduction (at least 75%) in the subsequent dose. Repeated systemic adverse reactions are sufficient reason for the cessation of further attempts to increase the dose.

In situations prompting dose reduction, a cautious increase in dose can be attempted once the reduced dose is tolerated. The dose should be reduced to the last level not causing the reaction and maintained at this level for two or three treatments before cautiously increasing again.

Prolonged period has elapsed since the last injection: Patients may lose tolerance for allergen injections during prolonged intervals (> 4 weeks) between doses. The duration of tolerance is an individual characteristic and varies from patient to patient. In general, the longer the lapse in the injection schedule, the greater dose reduction required.

Changing to a different lot of standardized extract: All extracts can lose allergenic activity over time and extracts vary in allergenic activity. Two different lots of extract could differ substantially in allergenic activity, even if they are the same formula and concentration. The volume of the first dose from the new vial should not exceed 50% of the previous dose. Do not use extracts beyond their expiry date.

Changing to an extract from a different manufacturer:Since manufacturing processes and sources of raw materials differ among manufacturers, the interchangeability of extracts from different manufacturers cannot be assured. Decrease the starting dose of the new extract when the extract is the same formula and dilution as the one previously used. In general, a volume dose reduction to 50% of the previous product dose is adequate, but each situation must be evaluated separately considering the patient's history of sensitivity, tolerance of previous injections, and other factors. If the patient tolerates the 50% decrease, then raise the next dose to the previous tolerated dose amount. To re‑establish the maintenance dose the starting interval between doses should not be greater than one week.

Changes made in the extract concentrate formula: Changes other than those listed above such as a difference in extracting fluid (e.g., change from non-glycerin extracts to 50% glycerin extracts), combining two or more stock concentrates, or any other change can affect a patient’s tolerance of the treatment. Extra dilutions are recommended whenever starting a revised formula. The greater the change, the greater the number of dilutions required.^23

Duration of Treatment

The duration of treatment for immunotherapy has not been established. A period of three to five years of injection therapy constitutes an average minimum course of treatment. Evaluate patients for treatment response at least every 6 to 12 months while they receive immunotherapy. The decision to continue or stop immunotherapy must be individualized.^23

3 DOSAGE FORMS AND STRENGTHS

Injection. Standardized mite extracts are labeled in Allergenic Units per milliliter (AU/mL) [see Description (11)]. Refer to the vial label for the product concentration [see How Supplied/Storage and Handling (16)].

- For percutaneous testing, standardized mite extract stock concentrates containing 30,000 AU/mL of D. farinae or D. pteronyssinus are supplied in 5 mL dropper vials [see Description (11)].
- For intradermal testing, standardized mite extract stock concentrates containing 30,000 AU/mL of D. farinae or D. pteronyssinus are supplied in 10 mL and 30 mL multidose vials [see Description (11)].
- For immunotherapy, standardized mite extract stock concentrates containing a total of 10,000 or 30,000 AU/mL of D. farinae or D. pteronyssinus or 5,000 or 15,000 AU/mL of an equal mixture of D. farinae and D. pteronyssinus are supplied in 10, 30, and 50 mL multiple-dose vials [see Description (11)].

4 CONTRAINDICATIONS

Standardized mite extracts are contraindicated in individuals with the following conditions:

- Severe, unstable or uncontrolled asthma.
- History of any severe systemic reaction to the allergen extract when administered for diagnosis or treatment.
- Medical conditions that reduce the ability to survive anaphylaxis.

5 WARNINGS AND PRECAUTIONS

5.1 Anaphylaxis

Anaphylaxis, which may lead to death, can occur in individuals following the administration of standardized mite extracts, particularly in the following situations [see Adverse Reactions (6)]: ^(18, 19, 20, 21)

- Extreme sensitivity to the standardized mite extracts.
- Receipt of an accelerated build-up schedule.
- Change from one lot of a particular standardized mite extract to another lot of the same standardized mite extract.
- Receipt of high doses of the standardized mite extracts.
- Exposure to excessive amounts of dust mite.

Standardized mite extracts may not be suitable for individuals who may be unresponsive to epinephrine or inhaled bronchodilators, such as those taking beta‑blockers.

Medications to treat systemic reactions, as well as emergency equipment should be available for immediate use. Administer standardized mite extracts in a healthcare setting under the supervision of a healthcare provider prepared to manage anaphylaxis. Individuals should remain in the provider’s office for a minimum of 30 minutes after receiving an injection of standardized mite extracts, so that any adverse reaction can be observed and appropriately managed.

6 ADVERSE REACTIONS

Common adverse reactions reported for standardized mite extracts are:

- Local reactions occurred in 26 to 82 % of all patients who received subcutaneous allergen immunotherapy, at the injection site (e.g., erythema, swelling, pruritus, tenderness and pain).^23
- Systemic adverse reactions, occurred in ≤ 7 % of patients who received subcutaneous allergen immunotherapy (e.g., generalized skin erythema, urticaria, pruritus, angioedema, rhinitis, wheezing, laryngeal edema, hypotension, and shock).^24 Systemic reactions may be fatal.^1, 23

No clinical trials of standardized mite extracts have been conducted.

Published studies of allergenic extracts report systemic reactions occurring in fewer than 1 % in patients receiving conventional immunotherapy and greater than 36 % in patients receiving rush immunotherapy.^1, 14, 26, 27 Most systemic reactions occurred within 30 minutes of injection. However, systemic reactions have been reported to occur up to 2 hours after the final injection with rush schedules. Some reactions have occurred up to 6 hours after skin tests or immunotherapy.^(23, 24, 28)

7 DRUG INTERACTIONS

7.1 Antihistamines

Do not perform skin testing with standardized mite extracts within 3 to 10 days of first-generation H1‑histamine receptor blockers (e.g., clemastine, diphenhydramine) and second-generation antihistamines (e.g., loratadine, fexofenadine) being used. These products suppress histamine skin test reactions and could mask a positive response.^2, 22, 23

7.2 Topical Corticosteroids and Topical Anesthetics

Topical corticosteroids may suppress skin reactivity; therefore, discontinue use at the skin test site for at least 2 to 3 weeks before skin testing.^2, ^3 Avoid use of topical local anesthetics at skin test sites because they can suppress flare responses.^4, 22, 23

7.3 Tricyclic Antidepressants

Tricyclic antidepressants, such as doxepin, can have potent antihistamine effects and may alter skin test results. Allow 7 to 14 days after discontinuation of tricyclic medication prior to skin testing.^(17, 22, 23)

See 17 for PATIENT COUNSELING INFORMATION.

8 USE IN SPECIFIC POPULATIONS

8.1 Pregnancy

Risk Summary

All pregnancies have a risk of birth defect, loss, or other adverse outcomes. In the U.S. general population, the estimated background risk of major birth defects and miscarriage in clinically recognized pregnancies is 2 to 4 % and 15 to 20 %, respectively. There are no human or animal data to establish the presence or absence of standardized mite extracts associated risks during pregnancy.^16

8.2 Lactation

Risk Summary

It is not known whether standardized mite extracts are present in human milk. Data are not available to assess the effects of these extracts on the breastfed child or on milk production/excretion. The developmental and health benefits of breastfeeding should be considered along with the mother’s clinical need for standardized mite extracts and any potential adverse effects on the breastfed child from the extracts or from the underlying maternal condition.

8.4 Pediatric Use

For use of these products in children younger than 5 years of age, consideration should be given to the patient’s ability to comply and cooperate with receipt of the product and the potential for difficulty in communicating with the child regarding systemic reactions.^(13, 23)

The volume of a dose for immunotherapy may need to be divided for pediatric patients [see Immunotherapy (2.3)].

8.5 Geriatric Use

Data are not available to determine if subjects 65 years of age and older respond differently to allergen immunotherapy than younger subjects.^15

11 DESCRIPTION

Standardized mite extracts are injections for percutaneous, intradermal, or subcutaneous use labeled in Allergy Units per milliliter (AU/mL).^5 Standardized Mite Extract (Dermatophagoides farinae), Standardized Mite Extract (Dermatophagoides pteronyssinus), and Standardized Mite Mixture Extract (Dermatophagoides farinae and Dermatophagoides pteronyssinus) are sterile solutions containing the extractables of D. farinae and/or D. pteronyssinus, 0.5 % sodium chloride, 0.275 % sodium bicarbonate, and 50 % glycerin by volume as a preservative. Source material for the extracts is the whole bodies of the mites. The mites are each grown on a medium of brine shrimp eggs and wheat germ, and are handled and cleaned in a manner such that the maximum carryover of the medium components is less than 1%. The medium contains no material of human origin.

Standardized Mite Extract (Dermatophagoides farinae) and Standardized Mite Extract (Dermatophagoides pteronyssinus) concentrates (stock concentrates) containing 30,000 AU/mL are supplied in dropper vials for percutaneous testing. Stock concentrates are also available in multiple-dose vials containing 10,000 AU/mL and 30,000 AU/mL to be diluted for intradermal testing and immunotherapy.

Standardized Mite Mixture Extract (Dermatophagoides farinae and Dermatophagoides pteronyssinus), is a mixture of the two mite species, in equal parts, resulting in D. pteronyssinus at 15,000 AU/mL and D. farinae at 15,000 AU/mL is available for therapeutic use. A mixture of the two species is also available at 5,000 AU/mL each species.

The potency of each lot of standardized mite extract is determined by comparison to the US reference preparation (10,000 AU/mL) provided by the Center for Biologics Evaluation and Research of the FDA. The relative potency of each extract is determined by ELISA inhibition and labeled in AU/mL.

12 CLINICAL PHARMACOLOGY

12.1 Mechanism of Action

The mechanisms of action of allergen immunotherapy have not been fully established.

13 NONCLINICAL TOXICOLOGY

13.1 Carcinogenesis, Mutagenesis, Impairment of Fertility

No studies in animals have been performed to evaluate carcinogenicity, mutagenicity or impairment of fertility.

14 CLINICAL STUDIES

Clinical studies that address the efficacy of immunotherapy are available.^(6, 7) Specific immunotherapy with allergenic extracts is helpful in reducing symptoms associated with exposure to the offending allergens. A summary of effectiveness by the Panel on Review of Allergenic Extracts, an advisory committee to the U.S. Food and Drug Administration, has been published.^25

15 REFERENCES

1. Lockey, Richard F., Linda M. Benedict, Paul C. Turkeltaub, Samuel C. Bukantz. Fatalities from immunotherapy (IT) and skin testing (ST). J. Allergy Clin. Immunol., 79 (4): 660-677, 1987.
2. Pipkorn, Ulf. Pharmacological influence of anti-allergic medication on In Vivo allergen testing. Allergy. 43: 81-86, 1988
3. Andersson, M. and U. Pipkorn. Inhibition of the dermal immediate allergic reaction through prolonged treatment with topical glucocorticosteroids. J. Allergy Clin. Immunol. 79 (2): 345-349, February 1987.
4. Pipkorn, Ulf, and M. Andersson. Topical dermal anesthesia inhibits the flare but not the wheal response to allergen and histamine in the skin prick test. Clinical Allergy. 17: 307-311, 1987.
5. Turkeltaub, Paul C., MD, and Suresh C. Rastogi, PhD. Quantitative intradermal test procedure for evaluation of subject sensitivity to standardized allergenic extracts and for assignment of allergy units to reference preparations using the ID50EAL method, Allergenics Products Testing Laboratory, Center for Biologics Evaluation and Research (CBER), FDA. Revised: November 1994.
6. Smith. A.P. Hyposensitization with Dermatophagoides pteronyssinus antigen: Trial in asthma induced by house dust. Br. Med. J., 4: 204-206, 1971.
7. Chapman, M.D., T.A.E. Platts-Mills, M. Gabriel, H.K. Ng, W.G.L. Allen, L.E. Hill, A.J. Nunn. Antibody response following prolonged hyposensitization with Dermatophagoides pteronyssinus extract. Int. Arch. Allergy Appl. Immunol., 61: 431-440, 1980.
8. Sheldon, J.M., R.G. Lovell, K.P. Matthews. A Manual of Clinical Allergy. Second Edition. W.B. Saunders, Philadelphia, 1967, pp. 107-112.
9. Sherman, W.B. Hypersensitivity Mechanism and Management. W.B. Sanders, Philadelphia, 1968, pp. 169-172.
10. Swineford, O. Asthma and Hay Fever. Charles C. Thomas, Springfield, IL, 1971, pp. 148-155.
11. Pauli, G., J.C. Bessot, R. Thierry, and A. Lamensons. Correlation between skin tests, inhalation tests and specific IgE in a study of 120 subjects to house dust and D. pteronyssinus. Clin. Allergy, 7:337, 1977.
12. Murray, A.B., A.C. Ferguson and B.J. Morrison. Diagnosis of house dust mite allergy in asthmatic children: what constitutes positive history? J. Allergy Clin. Immunol. 71:21, 1983.
13. Patterson, Roy, et al. Allergy Principles and Practice, 2nd ed. E. Middleton, Jr., C.E. Reed, E.F. Ellis, Ed., C.V. Mosby Co., 1983, St. Louis, MO, 1983, Chapter 52.
14. Turkeltaub, Paul C., MD, and Peter J. Gergen, MD. The risk of adverse reactions from percutaneous prick-puncture allergen skin testing, venipuncture, and body measurements: data from the second National Health and Nutrition Examination Survey, 1976-80 (NHANES II). J. Allergy Clin. Immunol. 84(6): 886-890, Dec. 1989.
15. Peebles, Ray Stokes, Jr., B. Bochner, Howard J. Zeitz, ed. Anaphylaxis in the elderly. Immunology and Allergy Clinics of North America. 13 (3): 627-646, August 1993.
16. Metzger, W.J., E. Turner and R. Patterson. The study of immunotherapy during pregnancy. J. Allergy Clin. Immunol. 61 (4): 268-272, 1978.
17. Rao, Kamineni S., et al. Duration of suppressive effect of tricyclic anti-depressants on histamine induced wheal and flare reactions on human skin. J. Allergy Clin. Immunol. 82: 752-757, November 1988.
18. Reid, M.J., R.F. Lockey, P.C. Turkletaub, T.A.E. Platts-Mills. Survey of fatalities from skin testing and immunotherapy. J. Allergy Clin. Immunol. 92 (1): 6-15, July 1993.
19. Reid, M.J., G. Gurka. Deaths associated with skin testing and immunotherapy. J. Allergy Clin. Immunol. 97 (1) Part 3:231, Abstract 195, January 1996.
20. Thompson, R.A. et al, report of a WHO/IUIS working group. The current status of allergen immunotherapy (hyposensitization). Allergy. 44: 369-379, 1989.
21. Malling, H.-J., B. Weeke, et al, The European Academy of Allergology and Clinical Immunology. Position Papers Allergy. 48 (Supplement 14): 9-82, 1993.
22. Bernstein IL, Li JT, Bernstein Dl, et al. Allergy diagnostic testing: an updated practice parameter. Ann Allergy Asthma Immunol. 2008 Mar;100:S1-148.
23. Cox L, Nelson H, Lockey R, Calabria C, Chacko T, Finegold I, et al. Allergen immunotherapy: A practice parameter third update. J Allergy Clin Immunol. 2011 Jan;127:S1-55.
24. Greineder DK. Risk management in allergen immunotherapy. J Allergy Clin Immunol. 1996 Dec;98(6 Pt 3):S3304
25. Federal Register Proposed Rule: Biological Products: Implementation of Efficacy Review, Allergenic Extracts, Federal Register 1985;50:3082-3288.
26. Lockey RF, Nicoara-Kasti GL, Theodoropoulos DS, Bukantz SC. Systemic reactions and fatalities associated with allergen immunotherapy. Ann Allergy Asthma Immunol 2001;87(suppl 1):47-55.
27. Malling HJ. Minimising the risks of allergen-specific injection immunotherapy. Drug Saf 2000;23:323-332.
28. Greenberg MA, Kaufman CR, Gonzalez GE, et. al. Late and immediate systemic-allergic reactions to inhalant allergen immunotherapy. J Allergy Clin Immunol 1986; 77:865-870.

16 HOW SUPPLIED/STORAGE AND HANDLING

16.1 How Supplied

Standardized mite extracts are supplied as 50 % glycerin stock concentrates labeled in Allergenic Units per Milliliter (AU/mL) and provided in 10 milliliter, 30 milliliter and 50 milliliter vials for use in percutaneous and intradermal skin testing and subcutaneous immunotherapy. These extracts may also be supplied in 5 milliliter dropper vials for percutaneous testing only. These products are supplied as listed in Table 2.

Table 2: Available Products

Available Products Name Allergenic Extracts | NDC | Vial Size
Standardized Mite, Dermatophagoides farinae 10,000 AU/mL | 65044-6723-2 | 10 mL
Standardized Mite, Dermatophagoides farinae 10,000 AU/mL | 65044-6723-4 | 50 mL
Standardized Mite, Dermatophagoides farinae 30,000 AU/mL | 65044-6720-1 | 5 mL
Standardized Mite, Dermatophagoides farinae 30,000 AU/mL | 65044-6720-2 | 10 mL
Standardized Mite, Dermatophagoides farinae 30,000 AU/mL | 65044-6720-3 | 30 mL
Standardized Mite, Dermatophagoides pteronyssinus 10,000 AU/mL | 65044-6695-2 | 10 mL
Standardized Mite, Dermatophagoides pteronyssinus 10,000 AU/mL | 65044-6695-4 | 50 mL
Standardized Mite, Dermatophagoides pteronyssinus 30,000 AU/mL | 65044-6692-1 | 5 mL
Standardized Mite, Dermatophagoides pteronyssinus 30,000 AU/mL | 65044-6692-2 | 10 mL
Standardized Mite, Dermatophagoides pteronyssinus 30,000 AU/mL | 65044-6692-3 | 30 mL
Standardized Mite Mix, Dermatophagoides farinae and Dermatophagoides pteronyssinus; 5,000 AU/mL (each species) | 65044-6691-2 | 10 mL
Standardized Mite Mix, Dermatophagoides farinae and Dermatophagoides pteronyssinus; 5,000 AU/mL (each species) | 65044-6691-4 | 50 mL
Standardized Mite Mix, Dermatophagoides farinae and Dermatophagoides pteronyssinus; 15,000 AU/mL (each species) | 65044-6690-2 | 10 mL
Standardized Mite Mix, Dermatophagoides farinae and Dermatophagoides pteronyssinus; 15,000 AU/mL (each species) | 65044-6690-3 | 30 mL

16.2 Storage and Handling

Store extracts at 2 °C to 8 °C (36 °F to 46 °F).

17 PATIENT COUNSELING INFORMATION

Instruct patients to remain in the office under observation for a minimum of 30 minutes after an injection or longer, if deemed necessary for the individual.

Inform patients that reactions may occur more than 30 minutes after skin testing or an injection.

Instruct patients to recognize the following symptoms as systemic adverse reactions and seek emergency medical care right away if any of these occur:

- Unusual swelling and/or tenderness at the injection site.
- Hives or itching of the skin.
- Swelling of face and/or mouth.
- Sneezing, coughing, or wheezing.
- Shortness of breath.
- Nausea.
- Dizziness or faintness.

Manufacturer:

Jubilant HollisterStier LLC

Spokane, WA 99207 U.S.A.

U.S. Lic. No. 1272

Version Date: 08/2024

345014-H08

PRINCIPAL DISPLAY PANEL

Mix of Standardized Mite 10 mL, 10k Carton Label
Mix of Standardized Mite 10 mL, 10k Vial Label
Mix of Standardized Mite 10 mL, 30k Carton Label
Mix of Standardized Mite 10 mL, 30k Vial Label
Mix of Standardized Mite 30 mL, 30k Carton Label
Mix of Standardized Mite 30 mL, 30k Vial Label

Mix of Standardized Mite 50 mL, 10k Vial Label
Mix of Standardized Mite 50 mL, 10k Carton Label

Standardized Mite, D. farinae 10 mL, 10k Carton Label
Standardized Mite, D. farinae 10 mL, 10k Vial Label
Standardized Mite, D. farinae 10 mL, 30k Carton Label
Standardized Mite, D. farinae 10 mL, 30k Vial Label
Standardized Mite, D. farinae 30 mL, 30k Carton Label
Standardized Mite, D. farinae 30 mL, 30k Vial Label
Standardized Mite, D. farinae 5 mL, 30k Carton Label
Standardized Mite, D. farinae 5 mL, 30k Vial Label

Standardized Mite, D. farinae 50 mL, 10k Vial Label
Standardized Mite, D. farinae 50 mL, 10k Carton Label

Standardized Mite, D. pter 10 mL, 10k Carton Label
Standardized Mite, D. pter 10 mL, 10k Vial Label
Standardized Mite, D. pter 10 mL, 30k Carton Label
Standardized Mite, D. pter 10 mL, 30k Vial Label
Standardized Mite, D. pter 30 mL, 30k Carton Label
Standardized Mite, D. pter 30 mL, 30k Vial Label
Standardized Mite, D. pter 5 mL, 30k Carton Label
Standardized Mite, D. pter 5 mL, 30k Vial Label

Standardized Mite, D. pter 50 mL, 10k Vial Label
Standardized Mite, D. pter 50 mL, 10k Carton Label